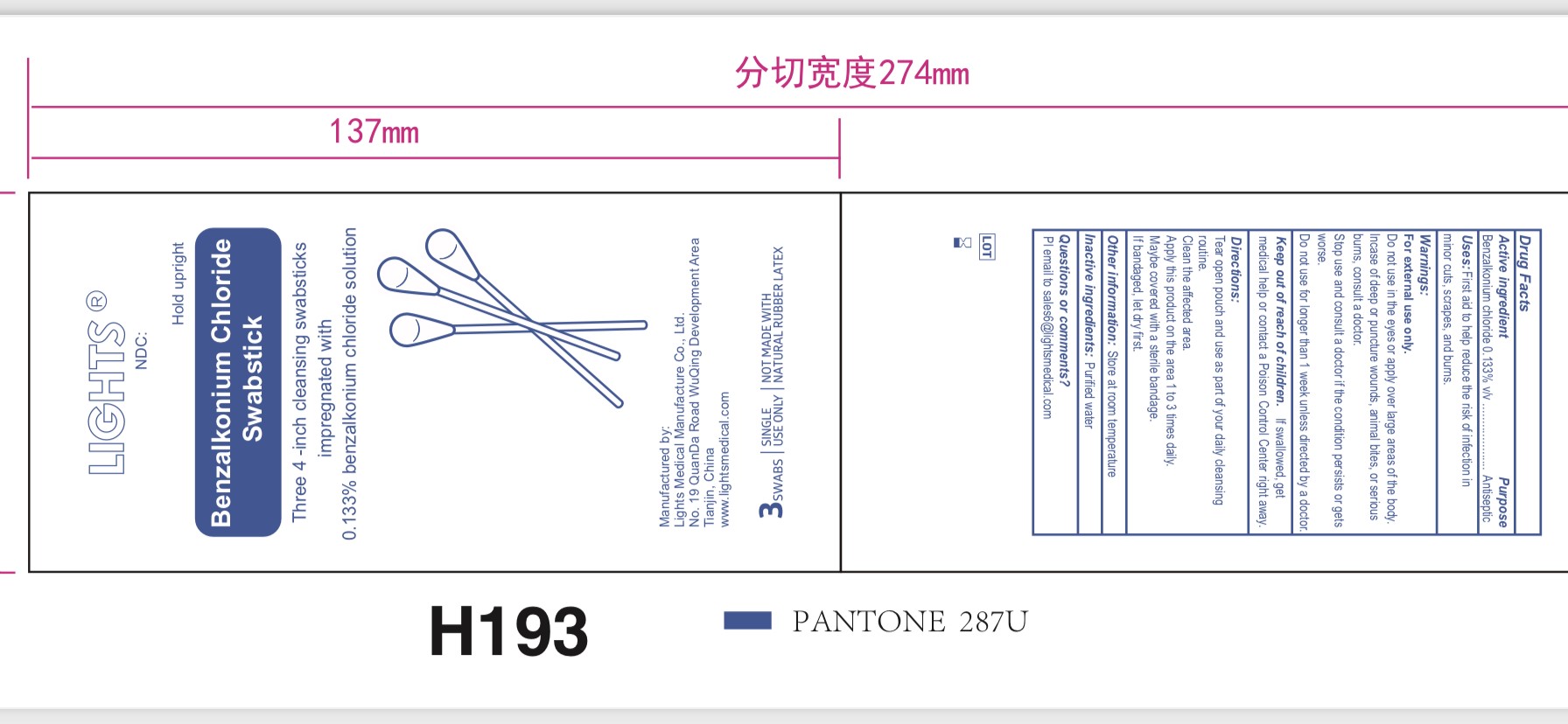 DRUG LABEL: LIGHTS Swabstick
NDC: 61333-208 | Form: SOLUTION
Manufacturer: Lights Medical Manufacture Co., Ltd.
Category: otc | Type: HUMAN OTC DRUG LABEL
Date: 20260121

ACTIVE INGREDIENTS: BENZALKONIUM CHLORIDE 0.133 g/100 g
INACTIVE INGREDIENTS: WATER

61333-208

Active ingredient

benzalkonium chloride 0.133%

Purpose

Antiseptic

Uses

First aid to help reduce the risk of infection in minor cuts, scrapes, and burns

Warnings

For external use only.

Do not use in the eyes or apply over over large areas of the body.

In case of deep or puncture wounds, animal bites, or serious burns, consult a doctor

Stop use and consult a doctor if condition persists or gets worse

Do not use for more than 1 week unless directed by a doctor.

Keep out of reach of children
If swallowed, get medical help or contact a Poison Control Center right away.

Directions

Tear open packet and use as part of your daily cleansing routine

Clean the affected area

Apply this product on area 1 to 3 times daily

Maybe covered by a sterile bandage

If bandaged, let dry first

INACTIVE INGREDIENT

Water

STORAGE AND HANDLING

Store at room temperature